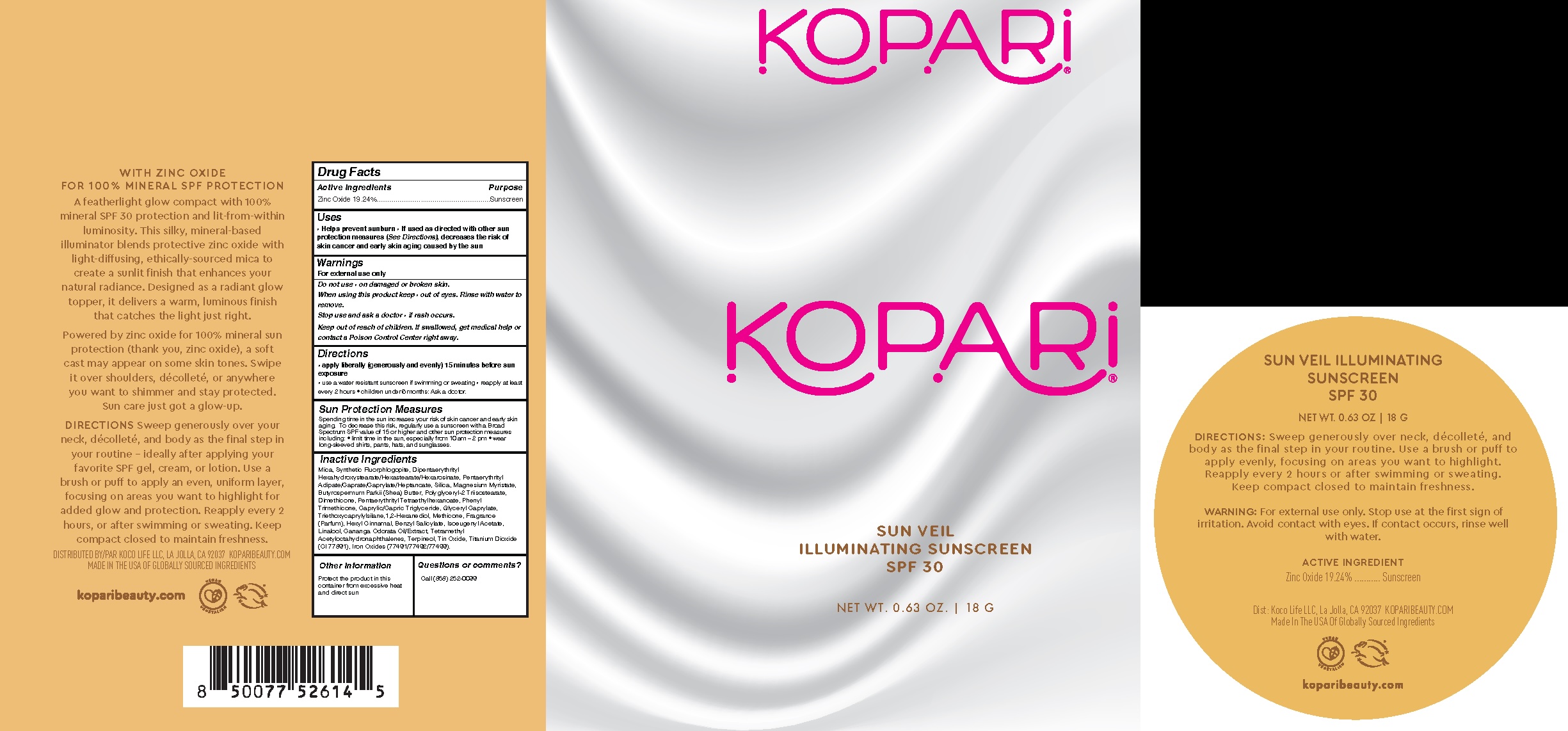 DRUG LABEL: Sun Veil Illuminating Sunscreen SPF30
NDC: 84130-018 | Form: POWDER
Manufacturer: Koco Life LLC
Category: otc | Type: HUMAN OTC DRUG LABEL
Date: 20251215

ACTIVE INGREDIENTS: ZINC OXIDE 19.24 g/100 g
INACTIVE INGREDIENTS: MAGNESIUM MYRISTATE; 1,2-HEXANEDIOL; TERPINEOL; TITANIUM DIOXIDE; MICA; TRIETHOXYCAPRYLYLSILANE; PENTAERYTHRITYL TETRAETHYLHEXANOATE; TETRAMETHYL ACETYLOCTAHYDRONAPHTHALENES; DIPENTAERYTHRITYL HEXAHYDROXYSTEARATE; BENZYL SALICYLATE; SILICA; METHICONE (20 CST); FERROUS OXIDE; YLANG-YLANG OIL; MAGNESIUM POTASSIUM ALUMINOSILICATE FLUORIDE; CAPRYLIC/CAPRIC TRIGLYCERIDE; ISOEUGENYL ACETATE; LINALOOL; PENTAERYTHRITYL ADIPATE/CAPRATE/CAPRYLATE/HEPTANOATE; SHEA BUTTER; DIMETHICONE; GLYCERYL CAPRYLATE; POLYGLYCERYL-2 TRIISOSTEARATE; HEXYL CINNAMAL; TIN OXIDE; PHENYL TRIMETHICONE

Sun Veil Illuminating Sunscreen SPF30

Active ingredient

Zinc oxide 19.24%

Purpose

Zinc oxide 19.24%.................Sunscreen

Uses

• Helps prevent sunburn

• If used as directed with other sunprotection measures (See Directions), decreases the risk ofskin cancer and early skin aging caused by the sun

Warnings

For external use only

Do not use • on damaged or broken skin.

When using this product keep • out of eyes. Rinse with water to remove.

Stop use and ask a doctor • if rash occurs.

Keep out of reach of children. If swallowed, get medical help or contact a Poison Control Center right away.

Directions

• apply liberally (generously and evenly) 15 minutes before sunexposure • use a water resistant sunscreen if swimming or sweating • reapply at leastevery 2 hours • children under 6 months: Ask a doctor.

Sun Protection Measures Spending time in the sun increases your risk of skin cancer and early skin aging. To decrease this risk, regularly use a sunscreen with a Broad Spectrum SPF value of 15 or higher and other sun protection measures including: • limit time in the sun, especially from 10 am – 2 pm • wear long-sleeved shirts, pants, hats, and sunglasses.

Inactive ingredients

Mica, Synthetic Fluorphlogopite, Dipentaerythrityl Hexahydroxystearate/Hexastearate/Hexarosinate, Pentaerythrityl Adipate/Caprate/Caprylate/Heptanoate, Silica, Magnesium Myristate, Butyrospermum Parkii (Shea) Butter, Polyglyceryl-2 Triisostearate, Dimethicone, Pentaerythrityl Tetraethylhexanoate, Phenyl Trimethicone, Caprylic/Capric Triglyceride, Glyceryl Caprylate, Triethoxycaprylylsilane,1,2-Hexanediol, Methicone, Fragrance (Parfum), Hexyl Cinnamal, Benzyl Salicylate, Isoeugenyl Acetate, Linalool, Cananga Odorata Oil/Extract, Tetramethyl Acetyloctahydronaphthalenes, Terpineol, Tin Oxide, Titanium Dioxide (CI 77891), Iron Oxides (77491/77492/77499)

Other information

Protect the product in this container from excessive heat and direct sun

Questions or comments?

Call (858) 252-0099

PACKAGE LABEL

Kopari

Sun Veil Illuminating Sunscreen SPF 30

Net Wt. 0.63 Oz. | 18 G